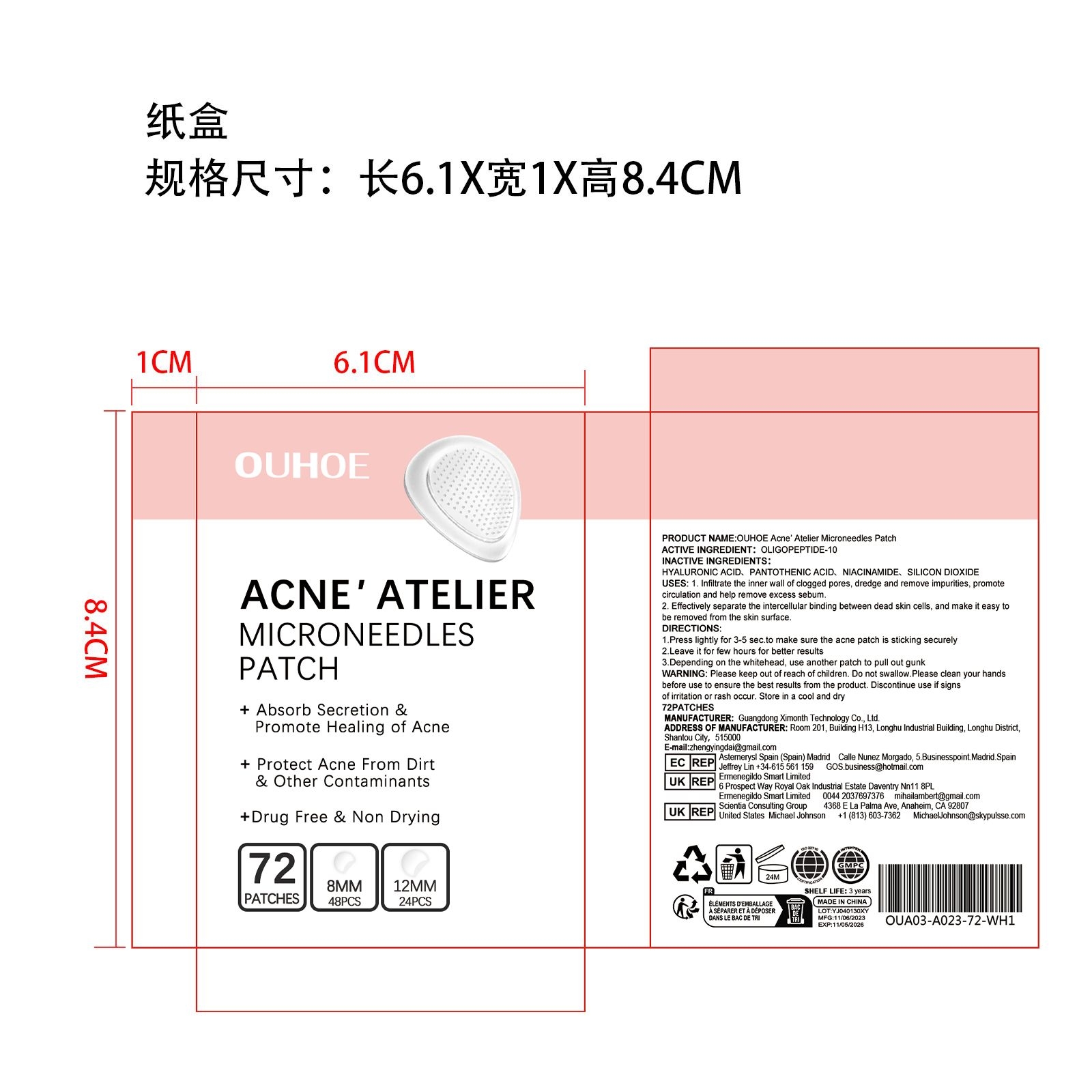 DRUG LABEL: OUHOE Acne Atelier Microneedles Patch
NDC: 84660-060 | Form: PATCH
Manufacturer: Guangdong Ximonth Technology Co., Ltd.
Category: otc | Type: HUMAN OTC DRUG LABEL
Date: 20241101

ACTIVE INGREDIENTS: OLIGOPEPTIDE-10 12 mg/72 mg
INACTIVE INGREDIENTS: SILICON DIOXIDE 15 mg/72 mg; PANTOTHENIC ACID 15 mg/72 mg; NIACINAMIDE 15 mg/72 mg; HYALURONIC ACID 15 mg/72 mg

Active Ingredient(s)

OLIGOPEPTIDE-10

Purpose

1. Infiltrate the inner wall of clogged pores, dredge and remove impurities, promote circulation and help remove excess sebum.
2. Effectively separate the intercellular binding between dead skin cells, and make it easy to be removed from the skin surface.

Use

1.Press lightly for 3-5 sec.to make sure the acne patch is sticking securely
2.Leave it for few hours for better results
3.Depending on the whitehead, use another patch to pull out gunk

WARNINGS

Please keep out of reach of children.Do not swallow.Please clean your hands before use to ensure the best results from the product.Discontinue use if signs of irritation or rash occur.Store in a cool and dry place.

DO NOT USE

Discontinue use if signs of irritation or rash occur.

Stop Use

Discontinue use if signs of irritation or rash occur.

KEEP OUT OF REACH OF CHILDREN

Please keep out of reach of children. Do not swallow.

SAFE HANDLING WARNING

Store in a cool and dry place.

INACTIVE INGREDIENT

HYALURONIC ACID、PANTOTHENIC ACID、NIACINAMIDE、SILICON DIOXIDE